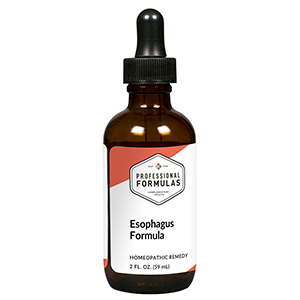 DRUG LABEL: Esophagus Formula
NDC: 63083-2101 | Form: LIQUID
Manufacturer: Professional Complementary Health Formulas
Category: homeopathic | Type: HUMAN OTC DRUG LABEL
Date: 20190815

ACTIVE INGREDIENTS: GLEDITSIA SINENSIS FRUIT 1 [hp_X]/59 mL; SALVIA MILTIORRHIZA ROOT 1 [hp_X]/59 mL; SCUTELLARIA BAICALENSIS ROOT 1 [hp_X]/59 mL; GINGER 1 [hp_X]/59 mL; ACHYRANTHES BIDENTATA ROOT 1 [hp_X]/59 mL; RHEUM OFFICINALE ROOT 1 [hp_X]/59 mL; AMMONIUM CATION 3 [hp_X]/59 mL
INACTIVE INGREDIENTS: ALCOHOL; WATER

C101

ACTIVE INGREDIENTS

Da-Zao 1X
Dan-Shen 1X
Huang-Qin 1X
Gan-Jiang 1X
Niu-Xi 1X
Da-Huang 1X, 6X
Ammonium nitricum 3X

QUESTIONS

Professional Formulas

PO Box 2034 Lake Oswego, OR 97035

INDICATIONS

For the temporary relief of belching, heartburn, nausea, minor discomfort in the upper abdomen, or dry cough.*

PURPOSE

*Claims based on traditional homeopathic practice, not accepted medical evidence. Not FDA evaluated.

WARNINGS

Consult a doctor if condition worsens or if symptoms persist. Keep out of the reach of children. In case of overdose, get medical help or contact a poison control center right away. If pregnant or breastfeeding, ask a healthcare professional before use.

Keep out of the reach of children.

PREGNANCY OR BREAST FEEDING

If pregnant or breastfeeding, ask a healthcare professional before use.

DIRECTIONS

Place drops under tongue 30 minutes before/after meals. Adults and children 12 years and over: Take 10 drops up to 3 times per day. Consult a physician for use in children under 12 years of age.

OTHER INFORMATION

Tamper resistant. If seal is broken, do not use. After opening, close container tightly and store at room temperature away from heat.

INACTIVE INGREDIENTS

20% ethanol, purified water.

LABEL

Est 1985

Professional Formulas

Complementary Health

Esophagus Formula

Homeopathic Remedy

2 FL. OZ. (59 mL)